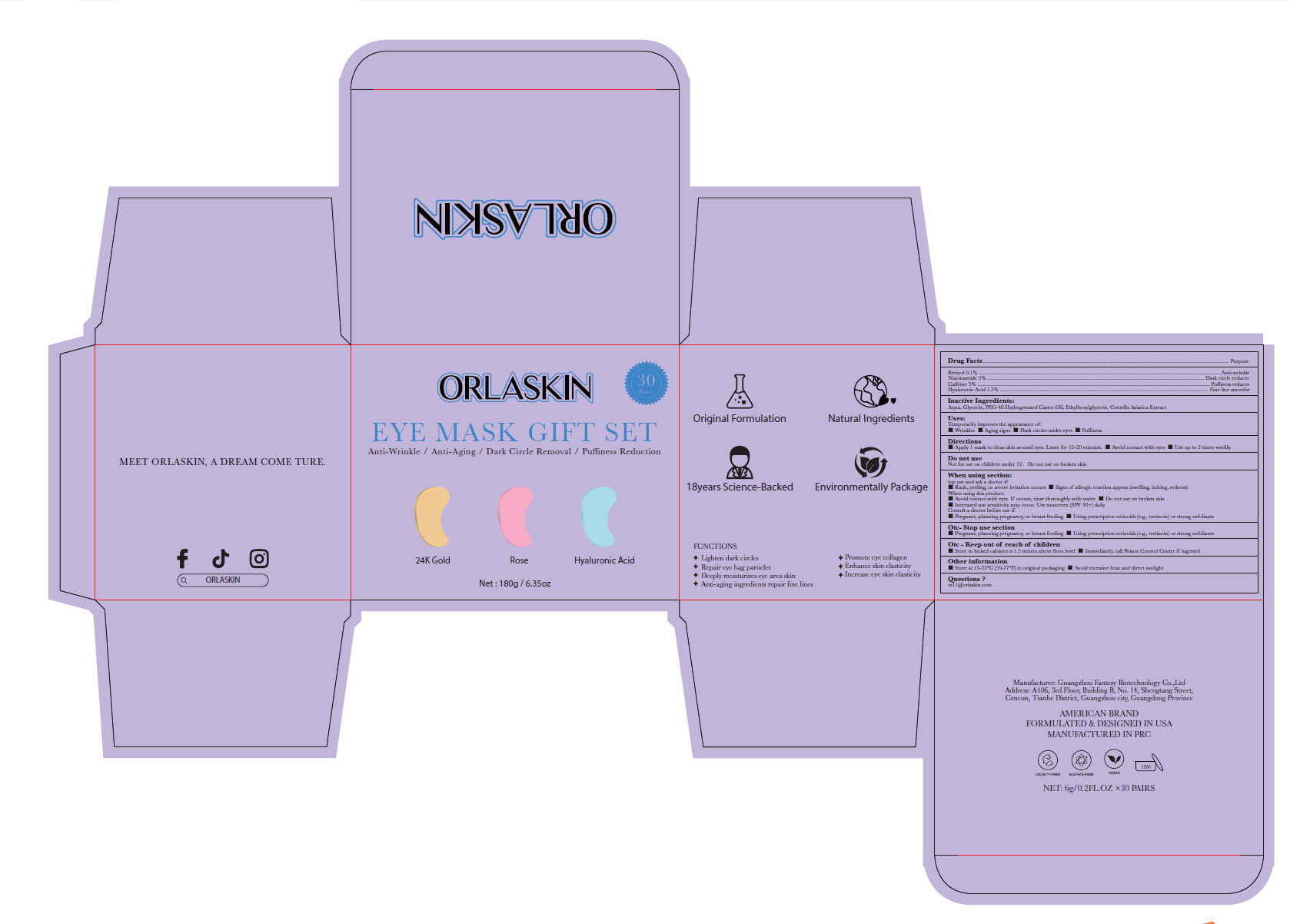 DRUG LABEL: ANTI-AGING EYE MASK
NDC: 84356-004 | Form: GEL
Manufacturer: Guangzhou Yapeng Refinement Chemical Co., Ltd.
Category: otc | Type: HUMAN OTC DRUG LABEL
Date: 20250617

ACTIVE INGREDIENTS: RETINOL 0.1 g/100 g; HYALURONIC ACID 1.5 g/100 g; CAFFEINE 3 g/100 g; NIACINAMIDE 5 g/100 g
INACTIVE INGREDIENTS: AQUA; GLYCERIN; CENTELLA ASIATICA TRITERPENOIDS; ETHYLHEXYLGLYCERIN; PEG-40 HYDROGENATED CASTOR OIL

84356-004

Active Ingredient(s)

Retinol 0.1%

Niacinamide 5%

Caffeine 3%

Hyaluronic Acid 1.5%

Purpose

Anti-wrinkle
Dark circle reducer
Puffiness reducer
Fine line smoothe

Use

Temporarily im proves the appearance of:
■Wrinkles ■Aging signs ■Dark circles under eyes ■Puffiness

Warnings

Do not use on injured wounds

Do not use

Not for use on children under 12. Do not use on broken skin

WHEN USING

top use and ask a doctor if:
1. Rash, peeling, or severe irritation occurs

2. Signs of allergic reaction appear (swelling, itching, redness) When using this product:

① Avoid contact with eyes. If occurs, rinse thoroughly with water

② Do not use on broken skin
3. Increased sun sensitivity may occur. Use sunscreen (SPF 30+) daily Consult a doctor before use if:
① Pregnant, planning pregnancy, or breast-feeding ② Using prescription retinoids (e.g., tretinoin) or strong exfoliants

STOP USE

Pregnant, planning pregnancy, or breast-feedingM [ J sing prescription retinoids (e.g, tretinoin) or strong exfoliants

KEEP OUT OF REACH OF CHILDREN

Store in locked cabinets≥1.5 meters above Aoor level Immediately call Poison Control Center if ingested

Directions

■ Apply l mask to clean skin around eyes. Leave for 15-20 minutes.

■ Avoid contact with eyes

■ Use up to 3 times weekly.

Other information

■Store at 15-25°C (59-77°F) in original packaging

■Avoid excessive heat and direct sunlight

Inactive ingredients

Aqua, Glycerin, Centella Asiatica Extract, Ethylhexylglycerin, PEG-40 Hydrogenated Castor Oil